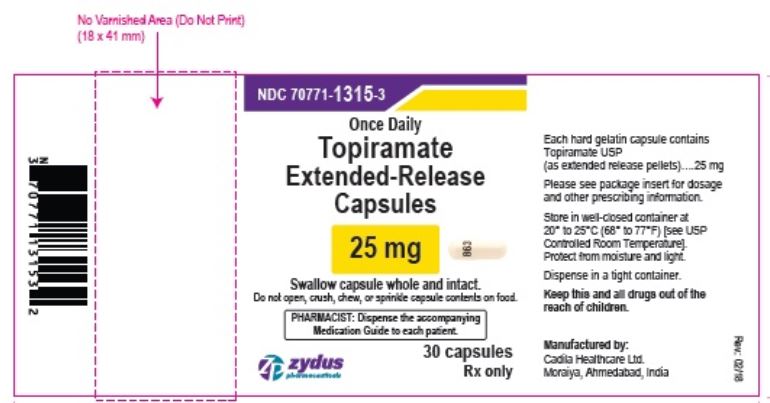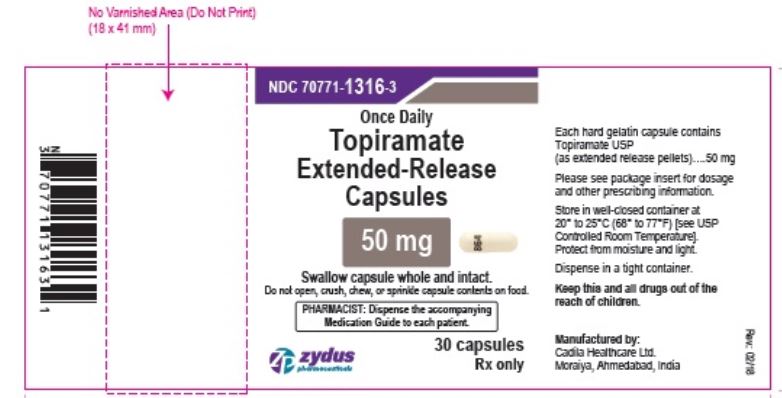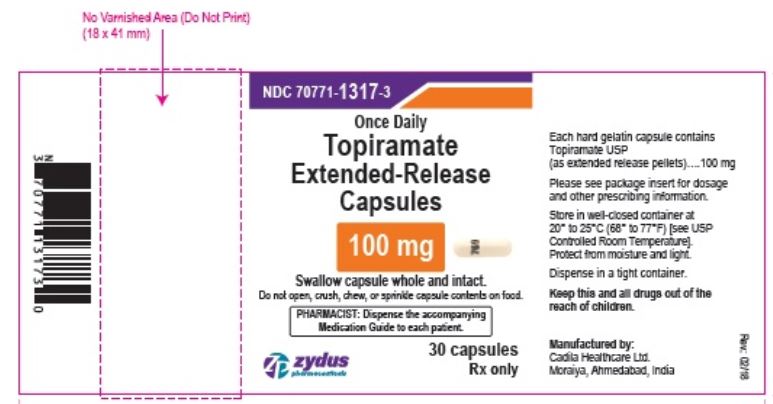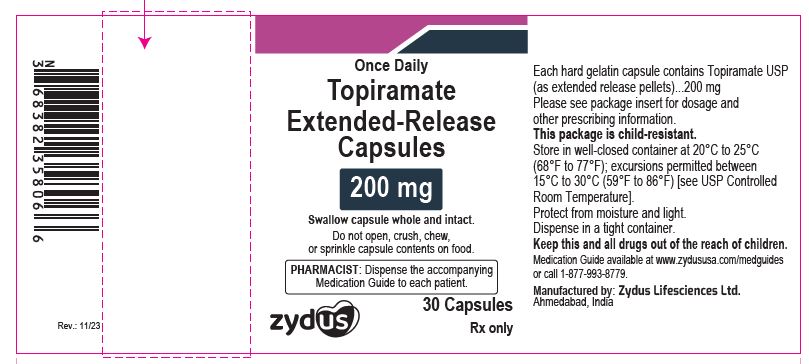 DRUG LABEL: Topiramate
NDC: 70771-1315 | Form: CAPSULE, EXTENDED RELEASE
Manufacturer: Zydus Lifesciences Limited
Category: prescription | Type: HUMAN PRESCRIPTION DRUG LABEL
Date: 20231108

ACTIVE INGREDIENTS: TOPIRAMATE 25 mg/1 1
INACTIVE INGREDIENTS: CELLULOSE, MICROCRYSTALLINE; ETHYLCELLULOSE, UNSPECIFIED; FERROSOFERRIC OXIDE; GELATIN; HYDROGENATED CASTOR OIL; HYPROMELLOSE, UNSPECIFIED; POLYETHYLENE GLYCOL, UNSPECIFIED; POTASSIUM HYDROXIDE; POVIDONE; PROPYLENE GLYCOL; SHELLAC; SODIUM LAURYL SULFATE; TALC; TITANIUM DIOXIDE; TRIETHYL CITRATE; WATER

TOPIRAMATE EXTENDED-RELEASE CAPSULES

PACKAGE LABEL.PRINCIPAL DISPLAY PANEL

NDC 70771-1315-3

Topiramate extended-release capsules, 25 mg

30 capsules

Rx only

NDC 70771-1316-3

Topiramate extended-release capsules, 50 mg

30 capsules

Rx only

NDC 70771-1317-3

Topiramate extended-release capsules, 100 mg

30 capsules

Rx only

NDC 70771-1858-3

Topiramate extended-release capsules, 200 mg

30 capsules

Rx only